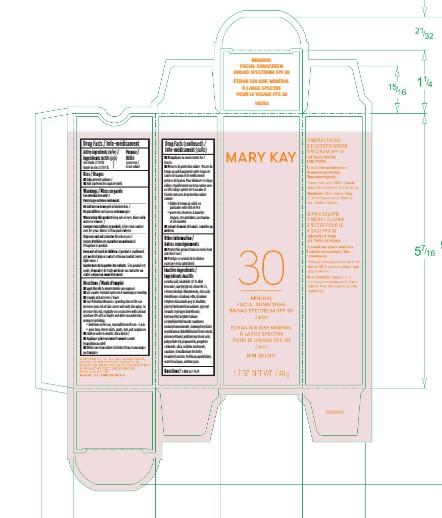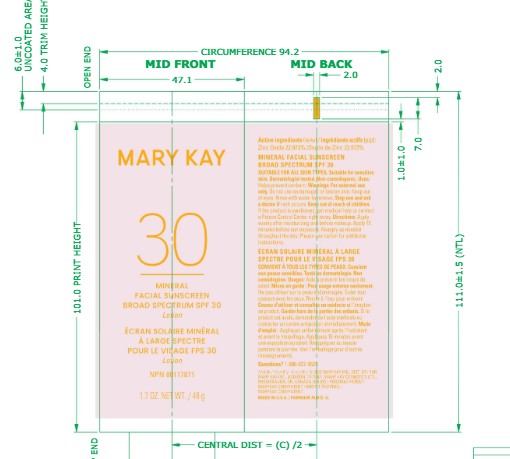 DRUG LABEL: Mary Kay Mineral Facial Sunscreen Broad Spectrum SPF30
NDC: 51531-3253 | Form: LOTION
Manufacturer: Mary Kay Inc.
Category: otc | Type: HUMAN OTC DRUG LABEL
Date: 20241217

ACTIVE INGREDIENTS: ZINC OXIDE 22.973 g/100 g
INACTIVE INGREDIENTS: HYDROGEN DIMETHICONE (13 CST); ASCORBIC ACID; DIMETHICONE; PHENOXYETHANOL; HYDROXYETHYL ACRYLATE/SODIUM ACRYLOYLDIMETHYL TAURATE COPOLYMER (45000 MPA.S AT 1%); CAPRYLYL GLYCOL; CHLORPHENESIN; LEVOMENOL; CETEARETH-25; SQUALANE; CETOSTEARYL ALCOHOL; CITRIC ACID MONOHYDRATE; EDETATE DISODIUM ANHYDROUS; DISODIUM ETHYLENE DICOCAMIDE PEG-15 DISULFATE; XANTHAN GUM; GLYCERYL BEHENATE/EICOSADIOATE; GLYCERYL MONOSTEARATE; ISONONYL ISONONANOATE; ISOPROPYL MYRISTATE; MYROTHAMNUS FLABELLIFOLIA LEAF; POLYSORBATE 60; POLYHYDROXYSTEARIC ACID (2300 MW); PROPANEDIOL; PROPYLENE CARBONATE; SILICON DIOXIDE; STEARALKONIUM HECTORITE; .ALPHA.-TOCOPHEROL ACETATE; TRIETHOXYCAPRYLYLSILANE; SORBITAN ISOSTEARATE; ALKYL (C12-15) BENZOATE; WATER

Mary Kay Mineral Facial Sunscreen Broad Spectrum SPF30

Active Ingredients

Zinc Oxide 22.973%

Purpose

Sunscreen

Uses

- helps prevent sunburn

Warnings

For external use only

Do not use

on damaged or broken skin

When using this product

keep out of eyes. Rinse with water to remove.

Stop use and ask a doctor

if rash occurs

Keep out of reach of children.

If product is swallowed, get medical help or contact a Poison Control Center right away.

Directions

- apply liberally 15 minutes before sun exposure
- use a water resistant sunscreen if swimming or sweating
- reapply at least every 2 hours
- Sun Protection Measures.Spending time in the sun increases your risk of skin cancer and early skin aging. To decrease this risk, regularly use a sunscreen with a broad spectrum SPF of 15 or higher and other sun protection measures including:
- limit time in the sun, especially from 10 a.m. - 2 p.m.
- wear long-sleeve shirts, pants, hats, and sunglasses
- children under 6 months: Ask a doctor

Inactive ingredients

ascorbic acid, bisabolol, c12-15 alkyl
benzoate, caprylyl glycol, ceteareth-25,
cetearyl alcohol, chlorphenesin, citric acid,
dimethicone, disodium edta, disodium
ethylene dicocamide peg-15 disulfate,
glyceryl behenate/eicosadioate, glyceryl
stearate, hydrogen dimethicone,
hydroxyethyl acrylate/sodium
acryloyldimethyl taurate copolymer,
isononyl isononanoate, isopropyl myristate,
myrothamnus ﬂabellifolia leaf/stem extract,
phenoxyethanol, polyhydroxystearic acid,
polysorbate 60, propanediol, propylene
carbonate, silica, sorbitan isostearate,
squalane, stearalkonium hectorite,
tocopheryl acetate, triethoxycaprylylsilane,
water/eau/aqua, xanthan gum.

Other information

- protect this product from excessive heat and direct sun

Questions or comments?

Questions? 1-800-627-9529

Principal Display Panel - 1.7 oz

Mary Kay

Mineral Facial Sunscreen

Broad Spectrum SPF 30

1.7 oz net wt/40 g

Mineral Sunscreen Carton

Mineral Sunscreen Tube